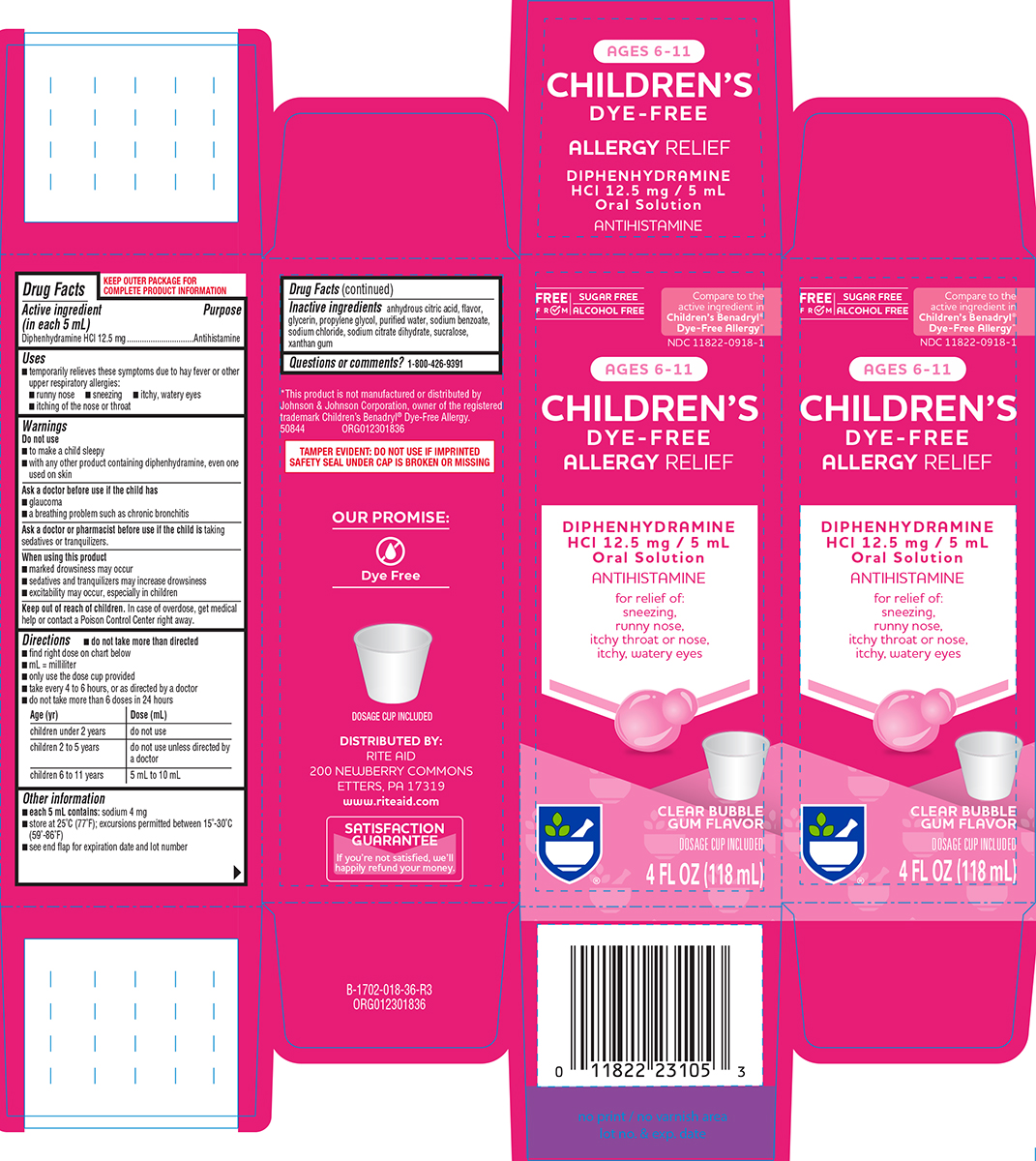 DRUG LABEL: Childrens Dye Free Allergy Relief
NDC: 11822-0918 | Form: SOLUTION
Manufacturer: Rite Aid Corporation
Category: otc | Type: HUMAN OTC DRUG LABEL
Date: 20250510

ACTIVE INGREDIENTS: DIPHENHYDRAMINE HYDROCHLORIDE 12.5 mg/5 mL
INACTIVE INGREDIENTS: ANHYDROUS CITRIC ACID; GLYCERIN; PROPYLENE GLYCOL; WATER; SODIUM BENZOATE; SODIUM CHLORIDE; TRISODIUM CITRATE DIHYDRATE; SUCRALOSE; XANTHAN GUM

Rite Aid 44-018

Active ingredient (in each 5 mL)

Diphenhydramine HCl 12.5 mg

Purpose

Antihistamine

Uses

- temporarily relieves these symptoms due to hay fever or other upper respiratory allergies:
  - runny nose
  - sneezing
  - itchy, watery eyes
  - itching of the nose or throat

Warnings

Do not use

- to make a child sleepy
- with any other product containing diphenhydramine, even one used on skin

Ask a doctor before use if the child has

- glaucoma
- a breathing problem such as chronic bronchitis

Ask a doctor or pharmacist before use if the child is

taking sedatives or tranquilizers.

When using this product

- marked drowsiness may occur
- sedatives and tranquilizers may increase drowsiness
- excitability may occur, especially in children

Keep out of reach of children.

In case of overdose, get medical help or contact a Poison Control Center right away.

Directions

- do not take more than directed
- find right dose on chart below
- mL = milliliter
- only use the dose cup provided
- take every 4 to 6 hours, or as directed by a doctor
- do not take more than 6 doses in 24 hours

Age (yr) | Dose (mL)
children under 2 years | do not use
children 2 to 5 years | do not use unless directed by a doctor
children 6 to 11 years | 5 mL to 10 mL

Other information

- each 5 mL contains: sodium 4 mg
- store at 25ºC (77ºF); excursions permitted between 15º-30ºC (59º-86ºF)
- see end flap for expiration date and lot number

Inactive ingredients

anhydrous citric acid, flavor, glycerin, propylene glycol, purified water, sodium benzoate, sodium chloride, sodium citrate dihydrate, sucralose, xanthan gum

Questions or comments?

1-800-426-9391

Principal Display Panel

FREE
FROM
SUGAR FREE
ALCOHOL FREE

Compare to the
active ingredient in
Children’s Benadryl®
Dye-Free Allergy*

NDC 11822-0918-1

AGES 6-11

CHILDREN’S
DYE-FREE
ALLERGY RELIEF

DIPHENHYDRAMINE
HCl 12.5 mg / 5 mL
Oral Solution
ANTIHISTAMINE

for relief of:
sneezing,
runny nose,
itchy throat or nose,
itchy, watery eyes

CLEAR BUBBLE
GUM FLAVOR

DOSAGE CUP INCLUDED

4 FL OZ (118 mL)

*This product is not manufactured or distributed by
Johnson & Johnson Corporation, owner of the registered
trademark Children’s Benadryl® Dye-Free Allergy.

50844 ORG012301836

TAMPER EVIDENT: DO NOT USE IF IMPRINTED
SAFETY SEAL UNDER CAP IS BROKEN OR MISSING

OUR PROMISE
Dye Free

DOSAGE CUP INCLUDED

DISTRIBUTED BY:
RITE AID
200 NEWBERRY COMMONS
ETTERS, PA 17319
www.riteaid.com

SATISFACTION
GUARANTEE
If you’re not satisfied, we’ll
happily refund your money.

Rite Aid 44-018